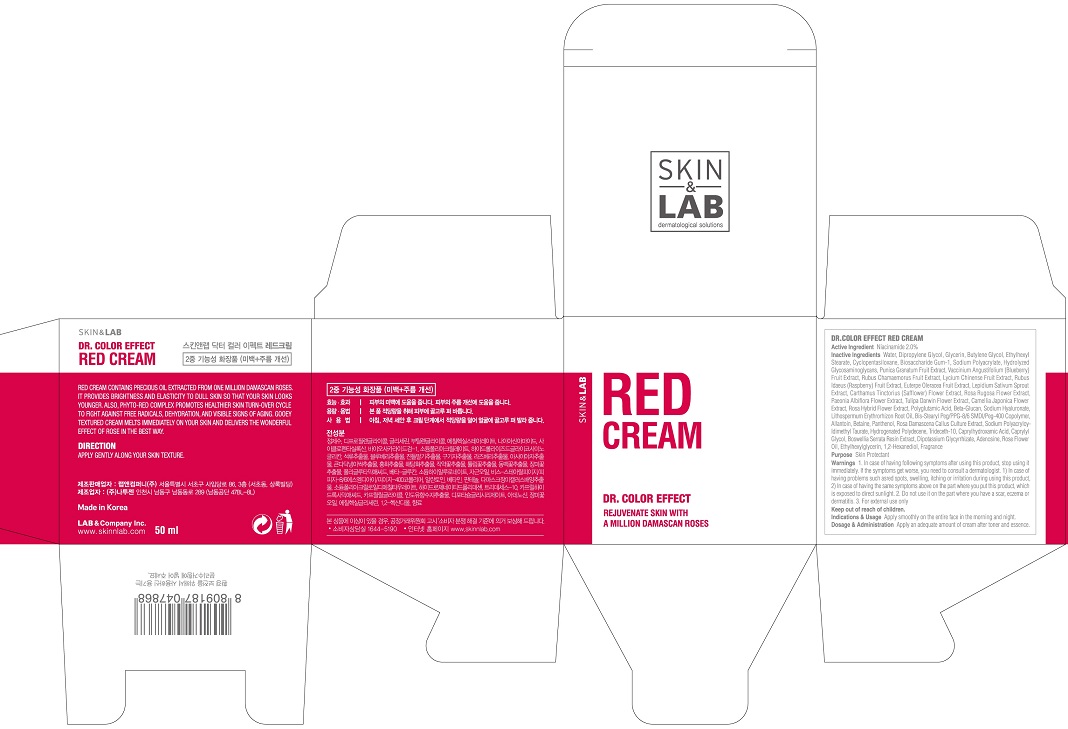 DRUG LABEL: DR. COLOR EFFECT RED
NDC: 69679-020 | Form: CREAM
Manufacturer: ES PURE VINE INC.
Category: otc | Type: HUMAN OTC DRUG LABEL
Date: 20160223

ACTIVE INGREDIENTS: NIACINAMIDE 1 g/50 mL
INACTIVE INGREDIENTS: FRAGARIN; VACCINIUM ANGUSTIFOLIUM LEAF; RUBUS CHAMAEMORUS FRUIT; LYCIUM CHINENSE FRUIT; RUBUS IDAEUS FRUIT VOLATILE OIL; LEPIDIUM SATIVUM WHOLE; ABELMOSCHUS MANIHOT FLOWER; PAEONIA SUFFRUTICOSA FLOWER OIL; TULIPA KAUFMANNIANA BULB; ADENOSINE; WATER; DIPROPYLENE GLYCOL; ROSA RUGOSA FLOWER; 1,4-DIPHENYL-1,3-BUTADIENE; ALLANTOIN; DIHYDROXYETHYL STEARAMINE OXIDE; PANTHENOL; ROSA DAMASCENA FLOWERING TOP; HYDROGENATED POLYDECENE (550 MW); TRIDECETH-10; CAPRYLHYDROXAMIC ACID; CAPRYLYL GLYCOL; INDIAN FRANKINCENSE; GLYCYRRHIZINATE DIPOTASSIUM; ETHYLHEXYLGLYCERIN; ETHYLENE GLYCOL; GLYCERIN; 1,3-BUTYLENE GLYCOL 1-PROPIONATE; ETHYLHEXYL STEARATE; DIMETHICONE CROSSPOLYMER (450000 MPA.S AT 12% IN CYCLOPENTASILOXANE); BIOSACCHARIDE GUM-1; SODIUM POLYACRYLATE (2500000 MW); HYDROLYZED GLYCOSAMINOGLYCANS (BOVINE; 50000 MW); POMEGRANATE; EUTERPE OLERACEA WHOLE; CARTHAMUS TINCTORIUS (SAFFLOWER) OLEOSOMES; CAMELLIA JAPONICA FLOWER OIL; GLATIRAMER ACETATE; ROSA RUGOSA FLOWER BUD; 1,2-HEXANEDIOL; ROSA CANINA WHOLE; POLYGALIC ACID; CURDLAN; PEG-9 DIGLYCIDYL ETHER/SODIUM HYALURONATE CROSSPOLYMER; LITHOSPERMUM ERYTHRORHIZON ROOT

ACTIVE INGREDIENT

Active Ingredient: Niacinamide 2.0%

INACTIVE INGREDIENT

Inactive Ingredients: Water, Dipropylene Glycol, Glycerin, Butylene Glycol, Ethylhexyl Stearate, Cyclopentasiloxane, Biosaccharide Gum-1, Sodium Polyacrylate, Hydrolyzed Glycosaminoglycans, Punica Granatum Fruit Extract, Vaccinium Angustifolium (Blueberry) Fruit Extract, Rubus Chamaemorus Fruit Extract, Lycium Chinense Fruit Extract, Rubus Idaeus (Raspberry) Fruit Extract, Euterpe Oleracea Fruit Extract, Lepidium Sativum Sprout Extract, Carthamus Tinctorius (Safflower) Flower Extract, Rosa Rugosa Flower Extract, Paeonia Albiflora Flower Extract, Tulipa Darwin Flower Extract, Camellia Japonica Flower Extract, Rosa Hybrid Flower Extract, Polyglutamic Acid, Beta-Glucan, Sodium Hyaluronate, Lithospermum Erythrorhizon Root Oil, Bis-Stearyl Peg/PPG-8/6 SMDI/Peg-400 Copolymer, Allantoin, Betaine, Panthenol, Rosa Damascena Callus Culture Extract, Sodium Polyacryloyldimethyl Taurate, Hydrogenated Polydecene, Trideceth-10, Caprylhydroxamic Acid, Caprylyl Glycol, Boswellia Serrata Resin Extract, Dipotassium Glycyrrhizate, Adenosine, Rose Flower Oil, Ethylhexylglycerin, 1,2-Hexanediol, Fragrance

PURPOSE

Purpose: Skin Protectant

WARNINGS

Warnings: 1. In case of having following symptoms after using this product, stop using it immediately. If the symptoms get worse, you need to consult a dermatologist. 1) In case of having problems such as red spots, swelling, itching or irritation during using this product, 2) In case of having the same symptoms above on the part where you put this product, which is exposed to direct sunlight. 2. Do not use it on the part where you have a scar, eczema or dermatitis. 3. For external use only

Keep out of reach of children: Keep out of reach of babies and children

INDICATIONS & USAGE

Indications & Usage: Apply smoothly on the entire face in the morning and night.

DOSAGE & ADMINISTRATION

Dosage & Administration: Take an adequate amount of this product after toner and essence. To feel stronger effect, please use it with RED SERUM